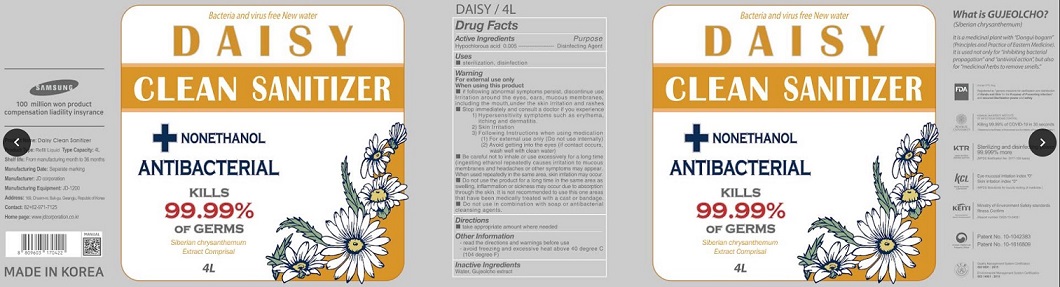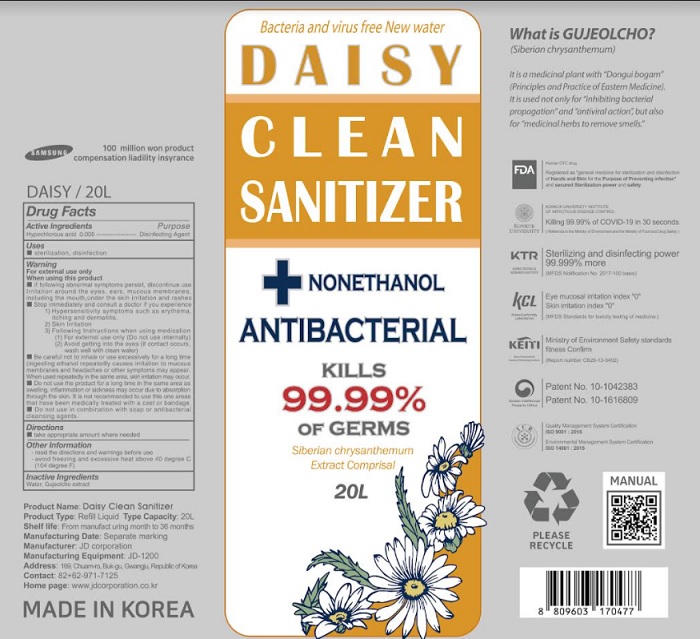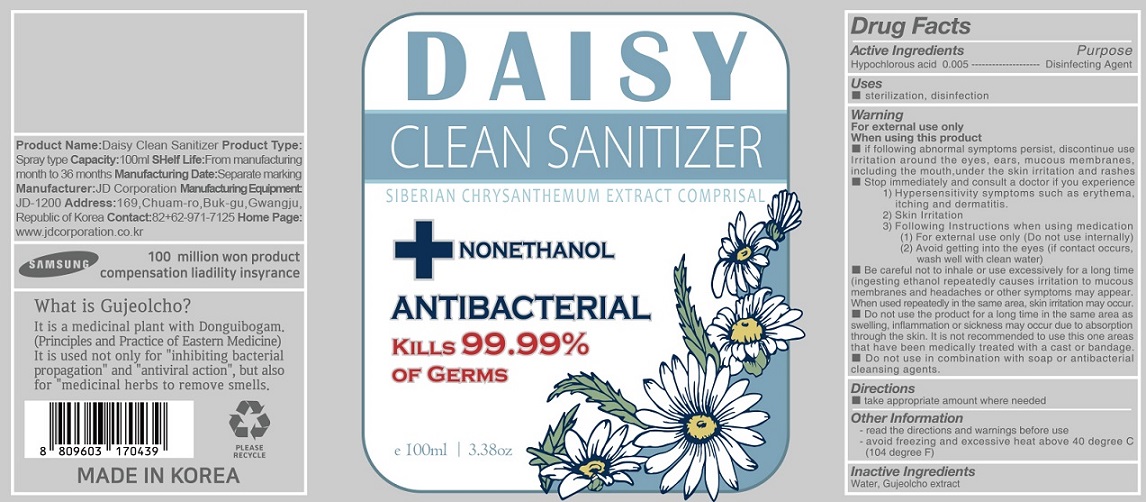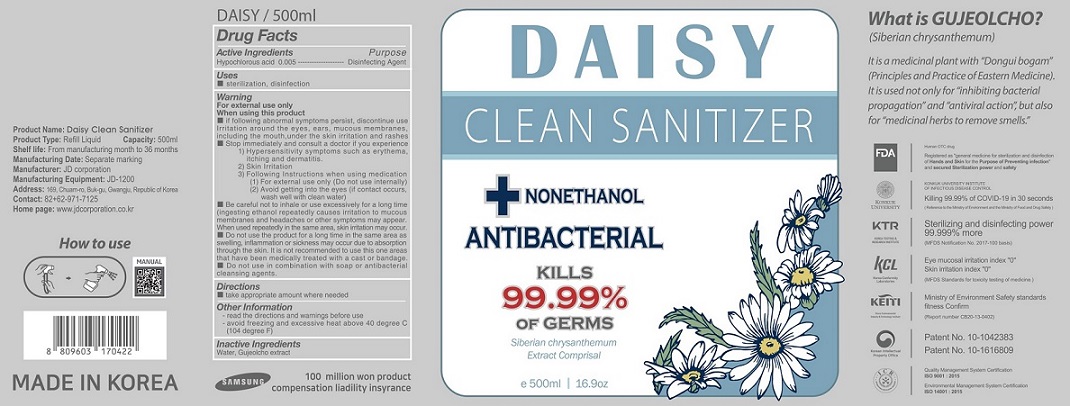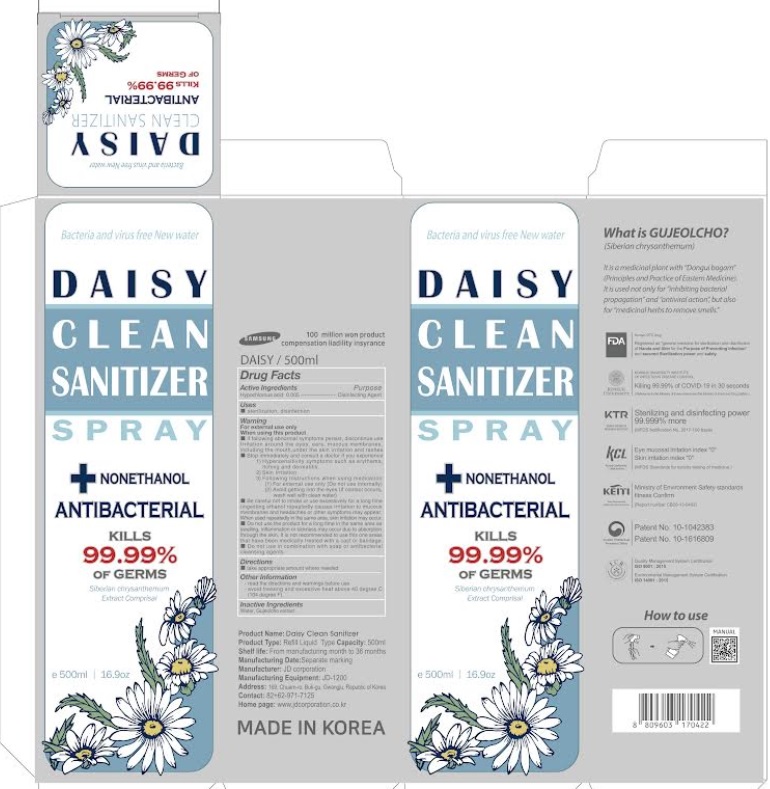 DRUG LABEL: DAISY CLEAN SANITIZER
NDC: 75696-0008 | Form: LIQUID
Manufacturer: JD corporation
Category: otc | Type: HUMAN OTC DRUG LABEL
Date: 20211006

ACTIVE INGREDIENTS: HYPOCHLOROUS ACID 0.005 g/100 mL
INACTIVE INGREDIENTS: WATER

Drug Facts

Active ingredient

hypochlorous acid 0.005

Purpose

Disinfecting agent

Uses

Sterilization, disinfection

Warning

For external use only
When using this product
• if followmg abnormal symptoms persist, discontinue use
Irritation around the eyes. ears, mucous membranes.
including the mouth.under the skin irritation and rashes
• Stop immediately and consult a doctor if you experience
1) Hypersensitivity symptoms such as erythema,
itching and dermatitis.
2) Skin Irritation
3) Following Instructions when using medication
(1) For external use only (Do not use internally)
(2) Avoid gelling into the eyes (if contact occurs,
wash well with clean water)
• Be careful not to inhale or use excessively for a long time
(ingesting ethanol repeatedly causes irritation to mucous
membranes and headaches or other symptoms may appear.
When used repeatedly in the same area, skin irritation may occur.
• Do not use the product for a tong time in the same area as
swelling, inflammation or sickness may occur due to absorption
through the skin. It is not recommended using this one area
that have been medically treated with a cast or bandage.
• Do not use in combination with soap or antibacterial
cleansing agents.

Directions

take appropriate amount where needed

Other information

read the directions and warnings before use

avoid freezing and excessive heat above 40 degree C (104 degree F)

Inactive ingredient

water, Gujeolcho extract